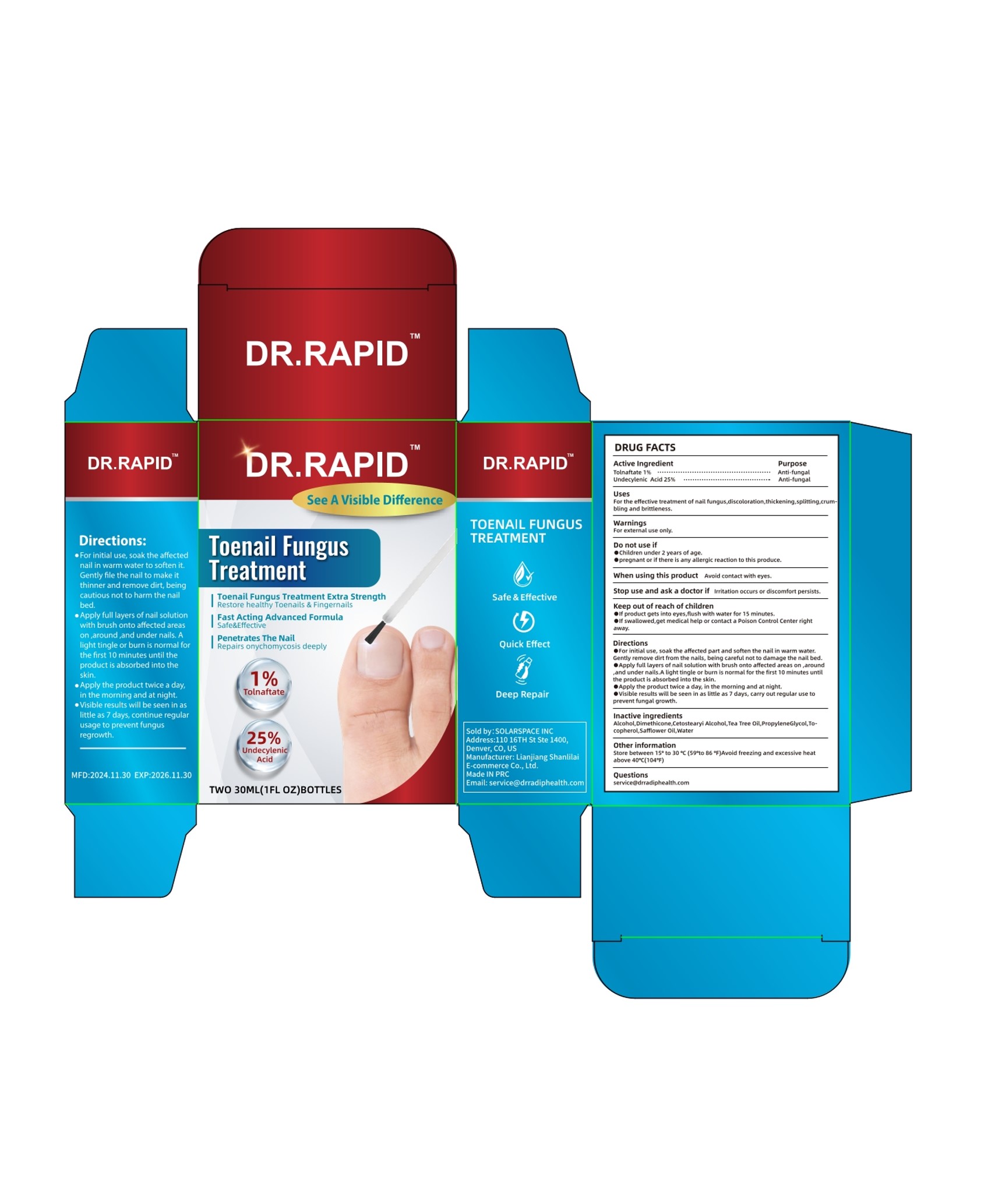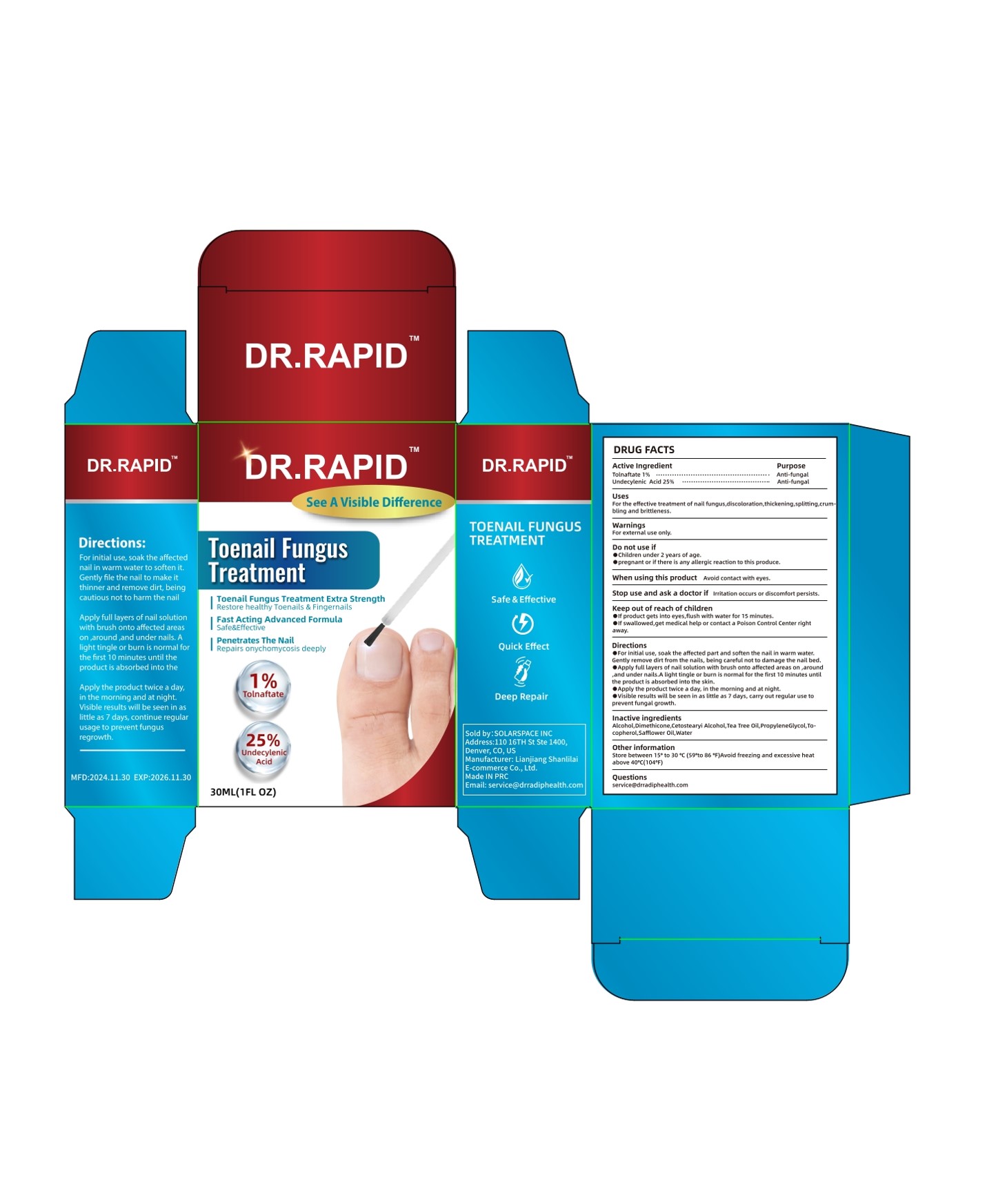 DRUG LABEL: TOENAIL FUNGUS TREATMENT  Liquid
NDC: 85038-002 | Form: LIQUID
Manufacturer: Lianjiang Shanlilai E-commerce Co., Ltd.
Category: otc | Type: HUMAN OTC DRUG LABEL
Date: 20241211

ACTIVE INGREDIENTS: UNDECYLENIC ACID 25 g/100 mL; TOLNAFTATE 1 g/100 mL
INACTIVE INGREDIENTS: CETOSTEARYL ALCOHOL; ALCOHOL; TEA TREE OIL; DIMETHICONE; WATER; PROPYLENE GLYCOL; SAFFLOWER OIL; TOCOPHEROL

TOENAIL FUNGUS TREATMENT Liquid

TOENAIL FUNGUS TREATMENT Liquid

ACTIVE INGREDIENT

TOLNAFTATE 1%
UNDECYLENIC ACID 25%

PURPOSE

Anti-fungal

INDICATIONS AND USAGE

For the effective treatment of nail fungus,discoloration,thickening,splitting,crum
bling and brittleness.

WARNINGS

For externat use only.

DO NOT USE

chlldren under 2 years of age.
pregnant or if there is any allergic reaction to this produce.

When using this product Avoid contact with eyes.

Stop use and ask a doctor if lrritation occurs or discomfort persists.

KEEP OUT OF REACH OF CHILDREN

oif product gets Into eyes,flush with water for 15 minutes.

if swallowred,get medical help or contact a Poison Control Center rightaway.

DOSAGE AND ADMINISTRATION

For initlal use, soak the affected part and soften the nalt in warm water.Gently remove dirt from the naiis, being careful not to damage the nail bed.
Apply full layers of nait solution with brush onto affected areas on ,around.and under nails,.A light tingle or burn is normal for the frst 10 minutes untilthe product is absorbed into the skin.
Apply the product twice a day, in the morning and at night.
Visible resuits will be seen in as little as 7 days, carry out regular use toprevent fungal growth.

STORAGE AND HANDLING

Store betwseen 15° to 30 ° C (59° to 86 ° F)Avoid freezing and excessive heat above 40° C(104° F)

INACTIVE INGREDIENT

ALCOHOL
DIMETHICONE
CETOSTEARYL ALCOHOL
TEA TREE OIL
PROPYLENE GLYCOL
TOCOPHEROL
SAFFLOWER OIL
WATER